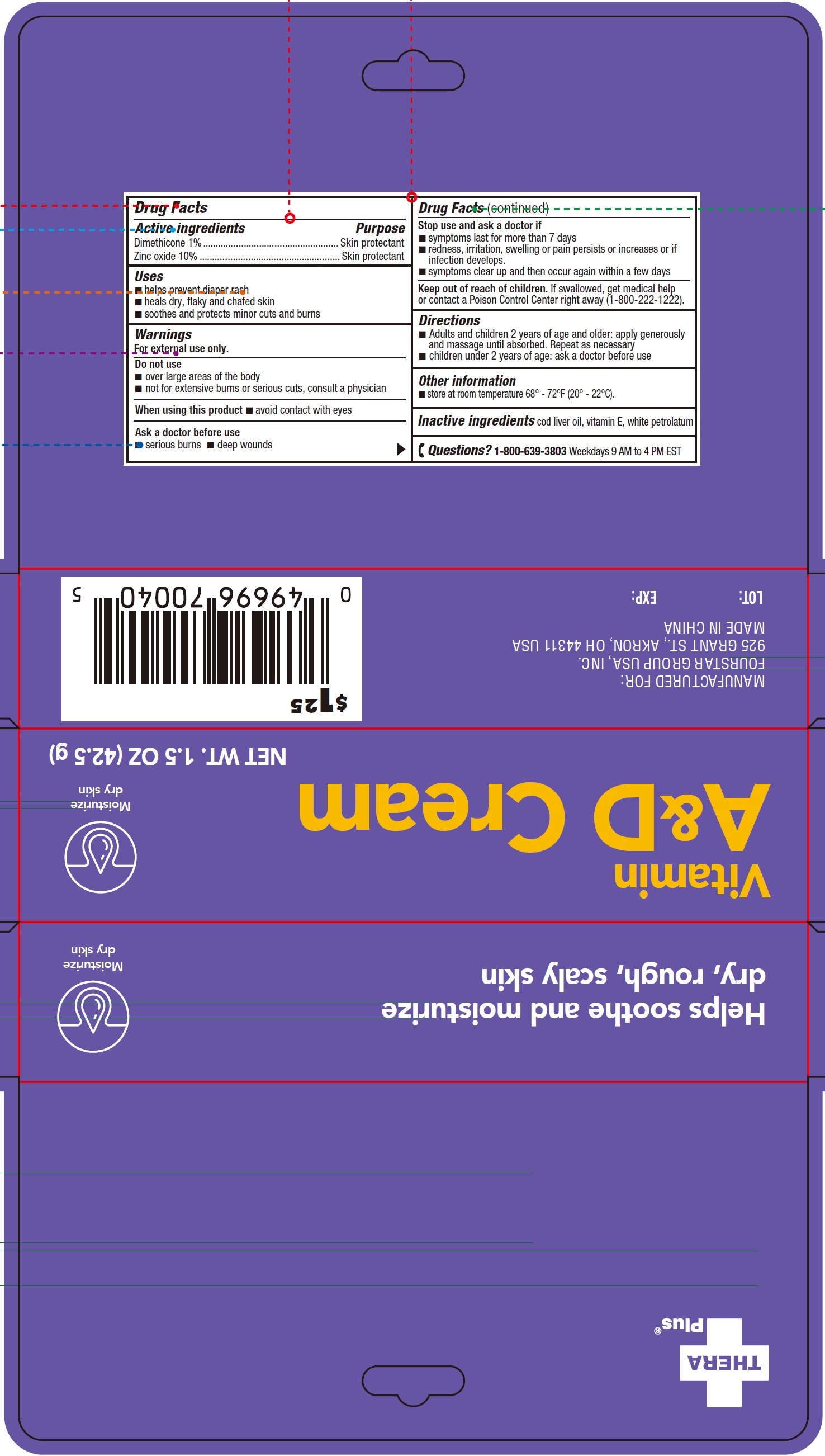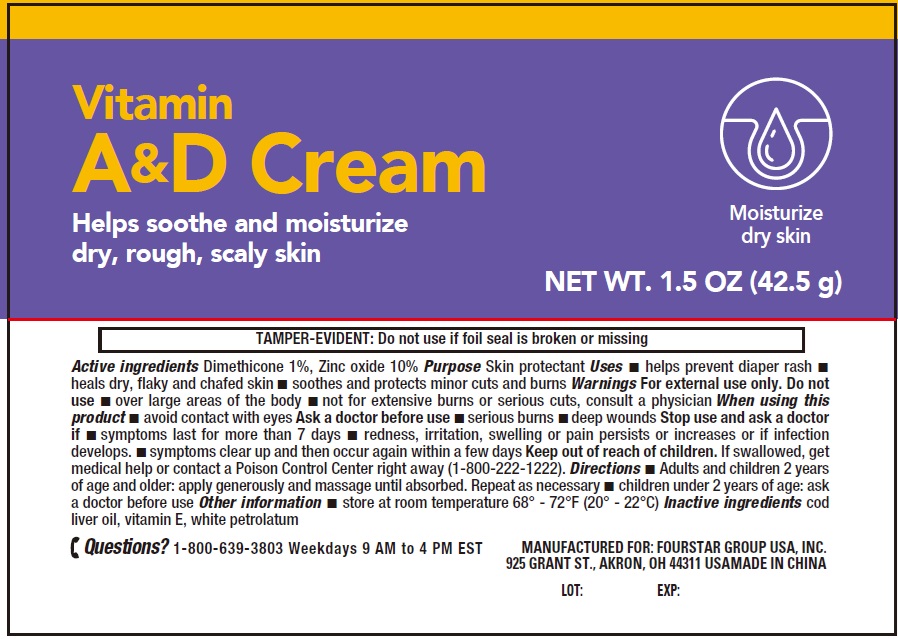 DRUG LABEL: Thera Plus Vitamin A and D Cream
NDC: 80684-135 | Form: CREAM
Manufacturer: FOURSTAR GROUP USA, INC.
Category: otc | Type: HUMAN OTC DRUG LABEL
Date: 20260202

ACTIVE INGREDIENTS: DIMETHICONE 10 mg/1 g; ZINC OXIDE 100 mg/1 g
INACTIVE INGREDIENTS: COD LIVER OIL; .ALPHA.-TOCOPHEROL; WHITE PETROLATUM

Thera Plus Vitamin A & D Cream

Active ingredients

Dimethicone 1%
Zinc oxide 10%

Purpose

Skin protectant

Uses

- helps prevent diaper rash
- heals dry, flaky and chafed skin
- soothes and protects minor cuts and burns

Warnings

For external use only.

Do not use

- over large areas of the body
- not for extensive burns or serious cuts, consult a physician

When using this product

- avoid contact with eyes

Ask a doctor before use

- serious burns
- deep wounds

Stop use and ask a doctor if

- symptoms last for more than 7 days
- redness, irritation, swelling or pain persists or increases or if infection develops.
- symptoms clear up and then occur again within a few days

Keep out of reach of children.

If swallowed, get medical help or contact a Poison Control Center right away (1-800-222-1222).

Directions

- Adults and children 2 years of age and older: apply generously and massage until absorbed. Repeat as necessary
- children under 2 years of age: ask a doctor before use

Other information

store at room temperature 68° - 72°F (20° - 22°C).

Inactive ingredients

cod liver oil, vitamin E, white petrolatum

Questions?

1-800-639-3803Weekdays 9 AM to 4 PM EST